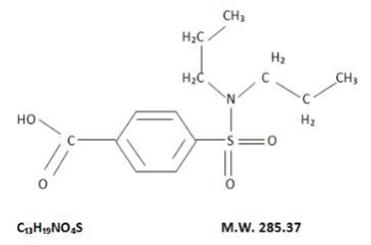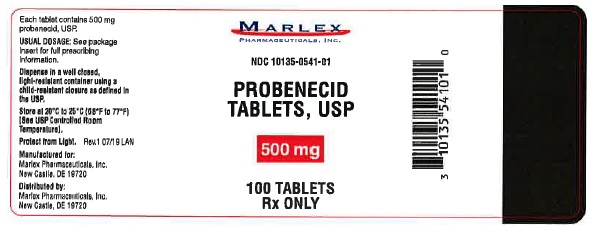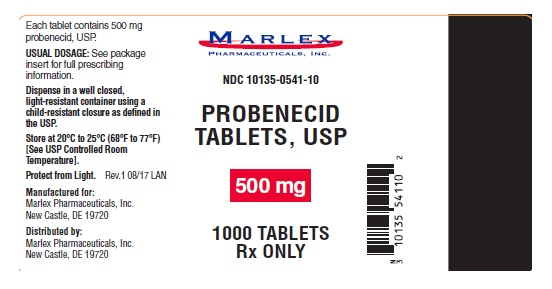 DRUG LABEL: Probenecid
NDC: 10135-541 | Form: TABLET, FILM COATED
Manufacturer: Marlex Pharmaceuticals Inc
Category: prescription | Type: HUMAN PRESCRIPTION DRUG LABEL
Date: 20251118

ACTIVE INGREDIENTS: PROBENECID 500 mg/1 1
INACTIVE INGREDIENTS: CELLULOSE, MICROCRYSTALLINE; SODIUM LAURYL SULFATE; SODIUM STARCH GLYCOLATE TYPE A POTATO; STARCH, CORN; POVIDONE K30; SILICON DIOXIDE; MAGNESIUM STEARATE; POLYVINYL ALCOHOL, UNSPECIFIED; TITANIUM DIOXIDE; POLYETHYLENE GLYCOL, UNSPECIFIED; TALC; D&C YELLOW NO. 10; FD&C YELLOW NO. 6; FD&C BLUE NO. 2; ALUMINUM OXIDE

PROBENECID

PROBENECID- probenecid tablet, film coated Marlex Pharmaceuticals Inc.

----------

Probenecid Tablets, USP

Probenecid Tablets, USP 500 mg

Rx only

DESCRIPTION:

Probenecid is a uricosuric and renal tubular transport blocking agent.

The chemical name for probenecid is 4-[(dipropylamino) sulfony1] benzoic acid. It has the following structural formula:

Probenecid, USP is a white or nearly white, fine, crystalline powder. Probenecid is soluble in dilute alkali, in alcohol, in chloroform, and in acetone; it is practically insoluble in water and in dilute acids.

Each tablet for oral administration contains 500 mg of probenecid and the following inactive ingredients: Microcrystalline cellulose, corn starch, sodium starch glycolate, povidone, colloidal silicon dioxide, magnesium stearate, sodium lauryl sulfate, polyvinyl alcohol, titanium dioxide, polyethylene glycol, talc, D&C Yellow #10 Aluminum Lake, FD&C Yellow #6 Aluminum Lake, and FD&C Blue #2 Aluminum Lake.

CLINICAL PHARMACOLOGY

Probenecid is a uricosuric and renal tubular blocking agent. It inhibits the tubular reabsorption of urate, thus increasing the urinary excretion of uric acid and decreasing serum urate levels. Effective uricosuria reduces the miscible urate pool, retards urate deposition, and promotes resorption of urate deposits.

Probenecid inhibits the tubular secretion of penicillin and usually increases penicillin plasma levels by any route the antibiotic is given. A 2-fold to 4-fold elevation has been demonstrated for various penicillins.

Probenecid also has been reported to inhibit the renal transport of many other compounds including aminohippuric acid (PAH), aminosalicylic acid (PAS), indomethacin, sodium iodomethamate and related iodinated organic acids, 17 –ketosteroids, pantothenic acid, phenolsulfonphthalein (PSP), sulfonamides, and sulfonylureas. See also Drug Interactions.

Probenecid decreases both hepatic and renal excretion of sulfobromophtalein (BSP). The tubular reabsorption of phosphorus is inhibited in hypoparathyroid but not in euparathyroid individuals.

Probenecid does not influence plasma concentrations of salicylates, nor the excretion of streptomycin, chloramphenicol, chlortetracycline, oxytetracycline, or neomycin.

INDICATIONS AND USAGE

Probenecid tablets are indicated for the treatment of the hyperuricemia associated with gout and gouty arthritis. As an adjuvant to therapy with penicillin or with ampicillin, methicillin, oxacillin, cloxacillin, or nafcillin, for elevation and prolongation of plasma levels by whatever route the antibiotic is given.

CONTRAINDICATIONS

Hypersensitivity to probenecid. Children under 2 years of age.

Not recommended in persons with known blood dyscrasias or uric acid kidney stones. Therapy with probenecid should not be started until an acute gouty attack has subsided.

WARNINGS

Exacerbation of gout following therapy with probenecid may occur; in such cases colchicine or other appropriate therapy is advisable.

Probenecid increases plasma concentrations of methotrexate in both animals and humans. In animal studies, increased methotrexate toxicity has been reported. If probenecid is given with methotrexate, the dosage of methotrexate should be reduced and serum levels may need to be monitored.

In patients on probenecid the use of salicylates in either small or large doses is contraindicated because it antagonizes the uricosuric action of probenecid. The biphasic action of salicylates in the renal tubules accounts for the so-called “paradoxical effect” of uricosuric agents. In patients on probenecid who require a mild analgesic agent the use of acetaminophen rather than small doses of salicylates would be preferred.

Rarely, severe allergic reactions and anaphylaxis have been reported with the use of probenecid. Most of these have been reported to occur within several hours after re-administration following prior usage of the drug.

The appearance of hypersensitivity reactions requires cessation of therapy with probenecid.

Use in Pregnancy:

Probenecid crosses the placenta barrier and appears in cord blood. The use of any drug in women of childbearing potential requires that the anticipated benefit be weighed against the possible hazards.

PRECAUTIONS

General:

Hematuria, renal colic, costovertebral pain, and formation of uric acid stones associated with the use of probenecid in gouty patients may be prevented by alkalization of the urine and a liberal fluid intake (see DOSAGE AND ADMINISTRATION). In these cases when alkali is administered, the acid-base balance of the patient should be watched.

Use with caution in patients with a history of peptic ulcer.

Probenecid has been used in patients with some renal impairment, but dosage requirements may be increased. Probenecid may not be effective in chronic renal insufficiency particularly when the glomerular filtration rate is 30 mL/minute or less. Because of its mechanism of action, probenecid is not recommended in conjunction with a penicillin in the presence of known renal impairment.

A reducing substance may appear in the urine of patients receiving probenecid. This disappears with discontinuance of therapy. Suspected glycosuria should be confirmed by using a test specific for glucose.

Drug Interactions:

When probenecid is used to elevate plasma concentrations of penicillin or other beta-lactams, or when such drugs are given to patients taking probenecid therapeutically, high plasma concentrations of the other drug may increase the incidence of adverse reactions associated with that drug. In the case of penicillin or other beta-lactams, psychic disturbances have been reported.

The use of salicylates antagonizes the uricosuric action of probenecid (see WARNINGS). The uricosuric action of probenecid is also antagonized by pyrazinamide.

Probenecid produces an insignificant increase in free sulfonamide plasma concentrations, but a significant increase in total sulfonamide plasma levels. Since probenecid decreases the renal excretion of conjugated sulfonamides, plasma concentrations of the latter should be determined from time to time when sulfonamide and probenecid are coadministered for prolonged periods. Probenecid may prolong or enhance the action of oral sulfonylureas and thereby increase the risk of hypoglycemia.

It has been reported that patients receiving probenecid require significantly less thiopental for induction of anesthesia. In addition, ketamine and thiopental anesthesia were significantly prolonged in rats receiving probenecid.

The concomitant administration of probenecid increases the mean plasma elimination half-life of a number of drugs which can lead to increased plasma concentrations. These include agents such as indomethacin, acetaminophen, naproxen, ketoprofen, meclofenamate, lorazepam, and rifampin. Although the clinical significance of this observation has not been established, a lower dosage of the drug may be required to produce a therapeutic effect, and increases a dosage of the drug in question should be made cautiously and in small increments when probenecid is being coadministered. Although specific instances of toxicity due to this potential interaction have not been observed to date, physicians should be alert to this possibility.

Probenecid given concomitantly with sulindac had only a slight effect on plasma sulfide levels, while plasma levels of sulindac and sulfone were increased. Sulindac was shown to produce a modest reduction in the uricosuric action of probenecid, which probably is not significant under most circumstances.

In animals and in humans, probenecid has been reported to increase plasma concentrations of methotrexate (see WARNINGS).

Falsely high readings for theophylline have been reported in an in vitro study, using the Schack and Waxler technique, when therapeutic concentrations of theophylline and probenecid were added to human plasma.

ADVERSE REACTIONS

The following adverse reactions have been observed and within each category are listed in order of decreasing severity.

Central Nervous System: headache, dizziness.

Metabolic: precipitation of acute gouty arthritis

Gastrointestinal: hepatic necrosis, vomiting, nausea, anorexia, sore gums.

Genitourinary: nephrotic syndrome, uric acid stones with or without hematuria, renal colic, costovertebral pain, and urinary frequency.

Hypersensitivity: anaphylaxis, fever, urticaria, pruritus

Hematologic: aplastic anemia, leukopenia, hemolytic anemia which in some patients could be related to genetic deficiency of glucose -6- phosphate dehydrogenase in red blood cells, anemia.

Integumentary: dermatitis, alopecia, flushing.

DOSAGE AND ADMINISTRATION

Gout:

Therapy with probenecid should not be started until an acute gouty attack has subsided. However, if an acute attack is precipitated during therapy, probenecid may be continued without changing the dosage, and full therapeutic dosage of colchicine, or other appropriate therapy, should be given to control the acute attack.

The recommended adult dosage is 250 mg (½ probenecid tablet), twice a day for one week, followed by 500 mg (1 tablet) twice a day thereafter.

Some degree of renal impairment may be present in patients with gout. A daily dosage of 1000 mg may be adequate. However, if necessary, the daily dosage may be increased by 500 mg increments every 4 weeks within tolerance (and usually not above 2000 mg per day) if symptoms of gouty arthritis are not controlled or the 24 hour uric acid excretion is not above 700 mg. As noted, probenecid may not be effective in chronic renal insufficiency particularly when the glomerular filtration rate is 30 mg mL/minute or less.

Gastric intolerance may be indicative of over dosage, and may be corrected by decreasing the dosage.

As uric acid tends to crystallize out of an acid urine, a liberal fluid intake is recommended, as well as sufficient sodium bicarbonate (3 to 7.5 g daily), or potassium citrate (7.5 g daily) to maintain an alkaline urine (see PRECAUTIONS).

Alkalization of the urine is recommended until the serum urate level returns to normal limits and tophaceous deposits disappear, i.e., during the period when urinary excretion of uric acid is at high level. Thereafter, alkalization of the urine and the usual restriction of purine-producing foods may be somewhat relaxed.

Probenecid should be continued at the dosage that will maintain normal serum urate levels. When acute attacks have been absent for 6 months or more and serum urate levels remain within normal limits, the daily dosage may be decreased by 500 mg every 6 months. The maintenance dosage should not be reduced to the point where serum urate levels tend to rise.

Probenecid and Penicillin Therapy (General):

Adults: The recommended dosage is 2000 mg (4 tablets of probenecid) daily in divided doses. This dosage should be reduced in older patients in whom renal impairment may be present.

Children: 2-14 years of age:

Initial dose: 25 mg/kg body weight (or 0.7 g/square meter body surface).

Maintenance Dose: 40 mg/kg body weight (or 1.2 g/square meter body surface) per day, divided into 4 doses.

For children weighing more than 50 kg (110lb) the adult dosage is recommended.

Probenecid is contraindicated in children under 2 years of age.

The PSP excretion test may be used to determine the effectiveness of probenecid in retarding penicillin excretion and maintaining therapeutic levels. The renal clearance of PSP is reduced to about one-fifth the normal rate when dosage of probenecid is adequate.

Penicillin Therapy (Gonorrhea) ¹

1 Recommended by the Center of Disease Control, U.S Department of Health and Human Services, Public Health Service (Morbidity and Mortality Weekly Report Supplement, Volume 34, Number 4S, October 18, 1985).

In uncomplicated gonococcal infections in men and women (urethral, cervical, rectal), 1 g of probenecid should be given orally with 4.8 million units of aqueous procaine penicillin G² (given IM), or 3 g of amoxicillin² (given orally), or 3.5 g of ampicillin² (given orally).

For further guidance, see CDC recommendations for definition of regimens of choice, alternative regimens, treatment of hypersensitive patients, and other aspects of therapy.

2 See package circulators of manufacturers for detailed information about CONTRAINDICATIONS, WARNINGS, PRECAUTIONS, and ADVERSE REACTIONS.

HOW SUPPLIED

Probenecid Tablets, USP are available containing 500 mg of Probenecid, USP.

The tablets are capsule shaped, film-coated yellow, debossed LCI on one side and 1367 on the other side. They are available as follows:

NDC 10135-0541-01 bottles of 100 tablets

NDC 10135-0541-10 bottles of 1000 tablets

STORE AT 20˚ to 25˚C (68˚-77˚F)[See USP Controlled Room Temperature]

PROTECT FROM LIGHT.

Dispense in a well closed, light-resistant container using a child-resistant closure as defined in the USP.

MANUFACTURED BY LANNETT COMPANY, INC. PHILADELPHIA, PA 19136

DISTRIBUTED BY

MARLEX PHARMACEUTICALS, INC. NEW CASTLE, DE 19720

Made in the USA

Rev.1 10/14LAN

PRINCIPAL DISPLAY PANEL

NDC 10135-541-01
Probenecid
Tablets, USP
500 mg
100 Tablets
Rx Only

PRINCIPAL DISPLAY PANEL

NDC 10135-541-10
Probenecid
Tablets, USP
500 mg
1000 Tablets
Rx Only